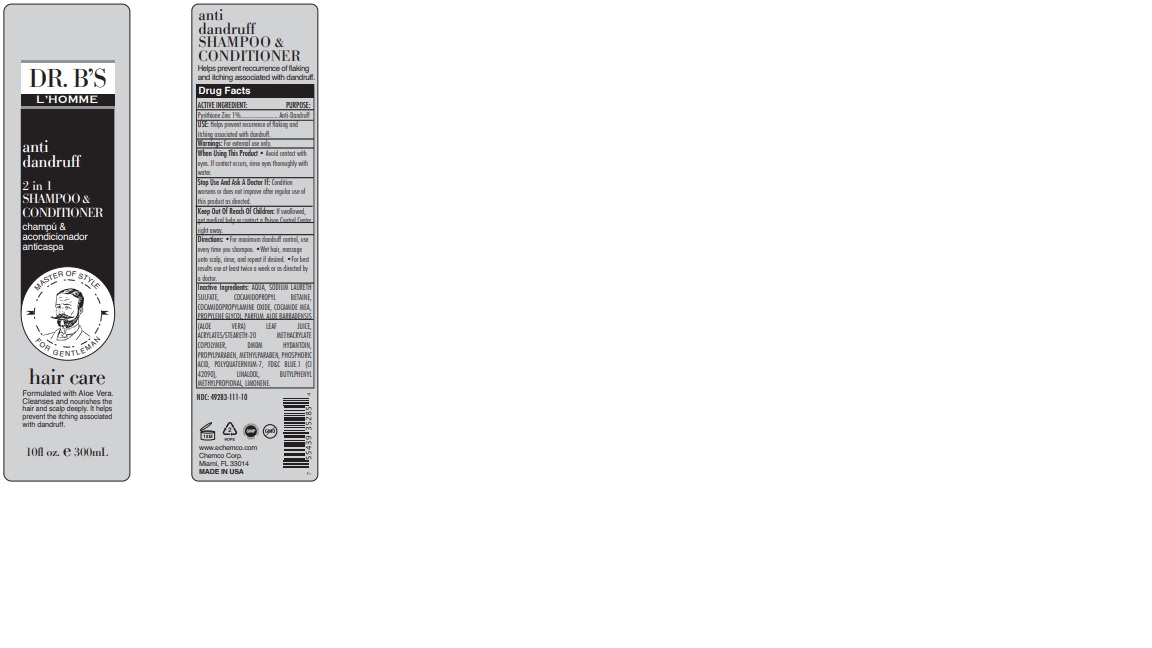 DRUG LABEL: Zinc Pyrithione
NDC: 49283-111 | Form: GEL
Manufacturer: CHEMCO CORPORATION
Category: otc | Type: HUMAN OTC DRUG LABEL
Date: 20210419

ACTIVE INGREDIENTS: PYRITHIONE ZINC 1 g/100 g
INACTIVE INGREDIENTS: SODIUM LAURETH SULFATE; COCAMIDOPROPYL BETAINE; COCAMIDOPROPYLAMINE OXIDE; ALOE VERA LEAF; PROPYLPARABEN; METHYLPARABEN; LINALOOL, (+/-)-; BUTYLPHENYL METHYLPROPIONAL; LIMONENE, (+/-)-; WATER; POLYQUATERNIUM-7 (70/30 ACRYLAMIDE/DADMAC; 900 KD); FD&C BLUE NO. 1; COCAMIDE; ETHYL ACRYLATE/METHACRYLIC ACID/STEARETH-20 METHACRYLATE COPOLYMER; DMDM HYDANTOIN; PHOSPHORIC ACID

49283-111-10